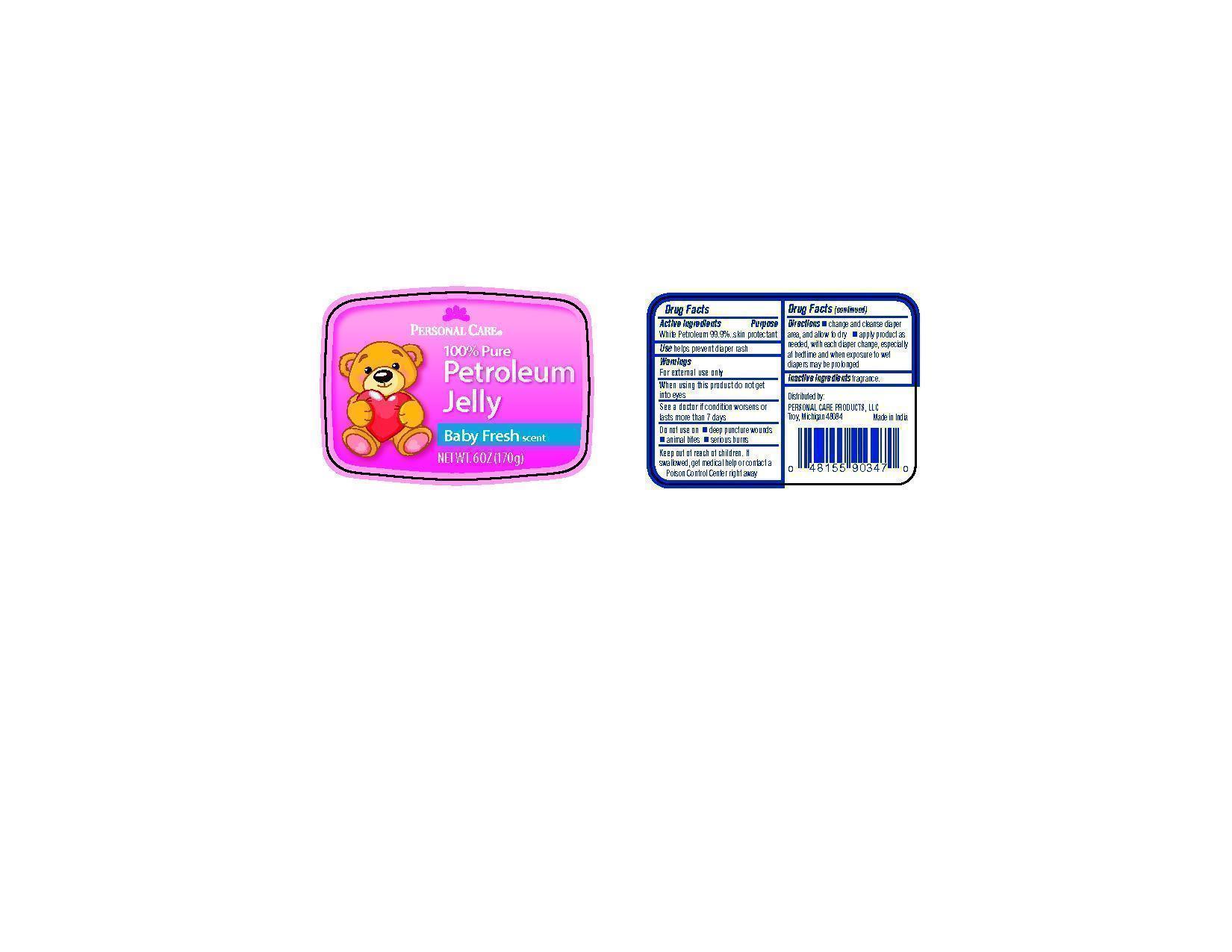 DRUG LABEL: Personal Care Petroleum
NDC: 29500-8030 | Form: JELLY
Manufacturer: Personal Care Products
Category: otc | Type: HUMAN OTC DRUG LABEL
Date: 20120629

ACTIVE INGREDIENTS: PETROLATUM 170 g/170 g

Personal Care Petroleum

Active ingredients White Petroleum 99.9%

Purpose skin protectant

Keep out of reach of children. If swallowed, get medical help or contact a Poison Control Center right away.

INDICATIONS AND USAGE

Use helps prevent diaper rash

Warnings

For external use only

When using this product do not get into eyes

See a doctor if condition worsens or lass more than 7 days

Do not use on deep puncture wounds, animal bites, serious burns.

Directions

change and cleanse diaper area and allow to dry

apply product as needed, with each diaper change, especially at bedtime and when exposure to wet diapers may be prolonged

Inactive ingredients fragrance

PACKAGE LABEL

Personal Care

100% Pure Petroleum Jelly

Baby Fresh scent

Net wt. 6 oz (170g)

Distributed by:
Personal Care Products, LLC

Troy, Michigan 48084

Made in India